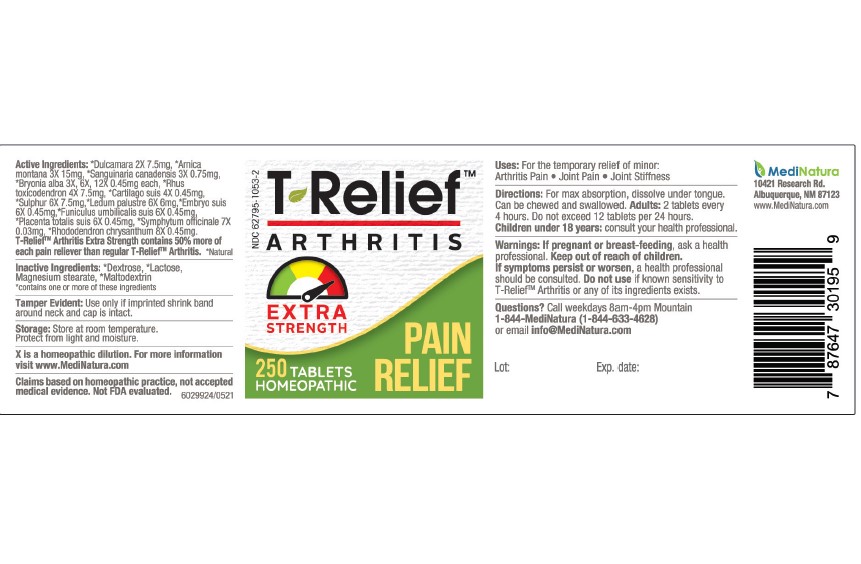 DRUG LABEL: T Relief Arthritis Extra Strength
NDC: 62795-1053 | Form: TABLET
Manufacturer: MediNatura Inc
Category: homeopathic | Type: HUMAN OTC DRUG LABEL
Date: 20230927

ACTIVE INGREDIENTS: ARNICA MONTANA 3 [hp_X]/1 1; BRYONIA ALBA ROOT 3 [hp_X]/1 1; SUS SCROFA CARTILAGE 4 [hp_X]/1 1; SOLANUM DULCAMARA TOP 2 [hp_X]/1 1; SUS SCROFA EMBRYO 6 [hp_X]/1 1; SUS SCROFA UMBILICAL CORD 6 [hp_X]/1 1; LEDUM PALUSTRE TWIG 6 [hp_X]/1 1; SUS SCROFA PLACENTA 6 [hp_X]/1 1; RHODODENDRON AUREUM LEAF 8 [hp_X]/1 1; TOXICODENDRON PUBESCENS LEAF 4 [hp_X]/1 1; SANGUINARIA CANADENSIS ROOT 3 [hp_X]/1 1; SULFUR 6 [hp_X]/1 1; COMFREY ROOT 7 [hp_X]/1 1
INACTIVE INGREDIENTS: DEXTROSE; MALTODEXTRIN; LACTOSE MONOHYDRATE; MAGNESIUM STEARATE

T Relief Arthritis Extra Strength

Warnings:

If pregnant or breast-feeding, ask a health
professional. Keep out of reach of children.
If symptoms persist or worsen, a health professional
should be consulted. Do not use if known sensitivity to
T-ReliefTM Arthritis or any of its ingredients exists.

Keep out of reach of children

Active Ingredients:

*Dulcamara 2X 7.5mg, *Arnica
montana 3X 15mg, *Sanguinaria canadensis 3X 0.75mg,
*Bryonia alba 3X, 6X, 12X 0.45mg each, *Rhus
toxicodendron 4X 7.5mg, *Cartilago suis 4X 0.45mg,
*Sulphur 6X 7.5mg,*Ledum palustre 6X 6mg,*Embryo suis
6X 0.45mg,*Funiculus umbilicalis suis 6X 0.45mg,
*Placenta totalis suis 6X 0.45mg, *Symphytum officinale 7X
0.03mg, *Rhododendron chrysanthum 8X 0.45mg.
T-ReliefTM Arthritis Extra Strength contains 50% more of
each pain reliever than regular T-ReliefTM Arthritis. *Natural

Uses:

For the temporary relief of minor:
Arthritis Pain • Joint Pain • Joint Stiffness

Inactive Ingredients:

*Dextrose, *Lactose,
Magnesium stearate, *Maltodextrin
*contains one or more of these ingredients

Purpose

PAIN RELIEF

Directions:

For max absorption, dissolve under tongue.
Can be chewed and swallowed. Adults: 2 tablets every
4 hours. Do not exceed 12 tablets per 24 hours.
Children under 18 years: consult your health professional